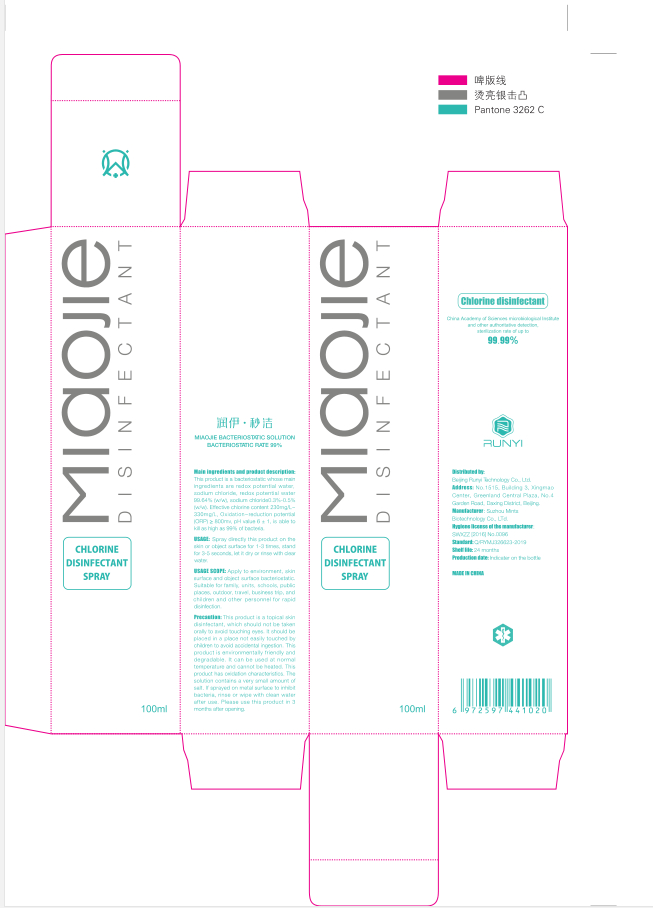 DRUG LABEL: RUNYI MIAOJIE Bacteriostatic solution
NDC: 41500-003 | Form: LIQUID
Manufacturer: Beijing Runyi Technology Co., Ltd
Category: otc | Type: HUMAN OTC DRUG LABEL
Date: 20200715

ACTIVE INGREDIENTS: HYPOCHLOROUS ACID 0.3 mg/100 mL
INACTIVE INGREDIENTS: WATER

KEEP OUT OF REACH OF CHILDREN SECTION

DOSAGE AND ADMINISTRATION

Colorless transparent liquid. Spray on intact skin surface for 3-5 seconds.

WARNINGS

Please read the drug instruction manual carefully and use as instructed or purchase and use under the guidance of a pharmacist

INACTIVE INGREDIENT

Water

INDICATIONS AND USAGE

Spray on intact skin surface for 3-5 seconds.

ACTIVE INGREDIENT

Hypochlorous acid